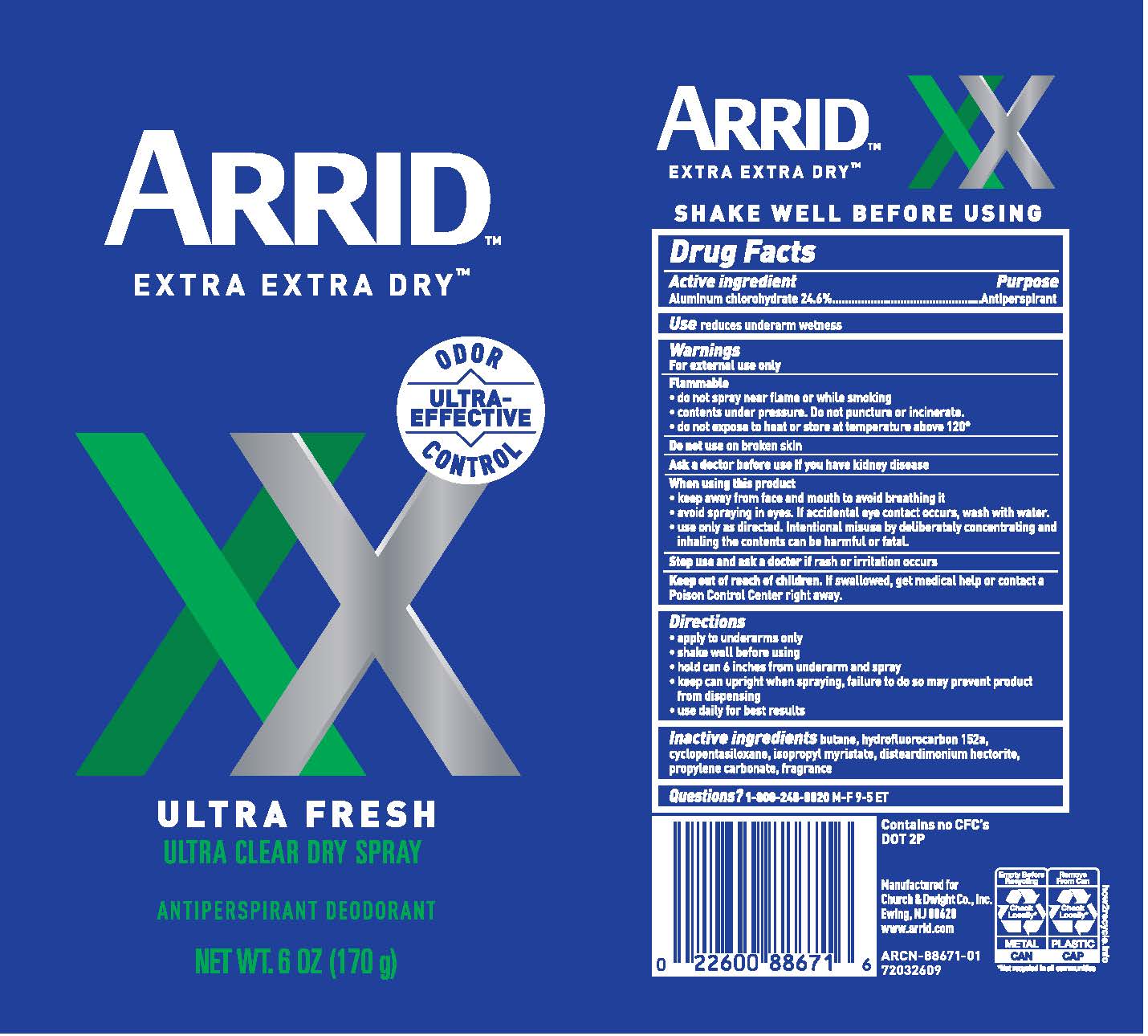 DRUG LABEL: Arrid Extra Extra Dry Ultra Fresh
NDC: 10237-859 | Form: AEROSOL, SPRAY
Manufacturer: Church & Dwight Co., Inc.
Category: otc | Type: HUMAN OTC DRUG LABEL
Date: 20251212

ACTIVE INGREDIENTS: ALUMINUM CHLOROHYDRATE 246 mg/1 g
INACTIVE INGREDIENTS: 1,1-DIFLUOROETHANE; CYCLOMETHICONE 5; ISOPROPYL MYRISTATE; DISTEARDIMONIUM HECTORITE; PROPYLENE CARBONATE

Arrid Extra Extra Dry Ultra Fresh Aerosol

Drug Facts

Active ingredient

Aluminum Chlorohydrate 24.6%

Purpose

Antiperspirant

Use

reduces underarm wetness

Warnings

For external use only

Flammable

- do not spray near flame or while smoking
- contents under pressure; do not puncture or incinerate
- do not expose to heat or store at temperatures above 120º

Do not use on broken skin

Ask a doctor before use if you have kidney disease.

When using this product

- keep away from face and mouth to avoid breathing it
- avoid spraying in eyes. If accidental eye contact occurs, wash with water.
- Use only as directed. Intentional misuse by deliberately concentrating and inhaling the contents can be harmful or fatal.

Stop use if rash or irritation occurs

Keep out of reach of children. If swallowed, get medical help or contact a Poison Control Center right away.

Directions

- apply to underarms only
- shake well before using
- hold can 6 inches from underarm and spray
- keep can upright when spraying, failure to do so may prevent product from dispensing
- use daily for best results

Inactive ingredients

butane, hydrofluorocarbon 152a, cyclopentasiloxane, isopropyl myristate, disteardimonium hectorite, propylene carbonate, fragrance

QUESTIONS

Questions? 1-800-248-8820 M-F 9-5 ET

PACKAGE LABEL

ARRID

EXTRA EXTRA DRY

XX

ULTRA-EFFECTIVE ODOR CONTROL

ULTRA FRESH

ULTRA CLEAR DRY SPRAY

ANTIPERSPIRANT DEODORANT

NET WT. 6 OZ. (170g)